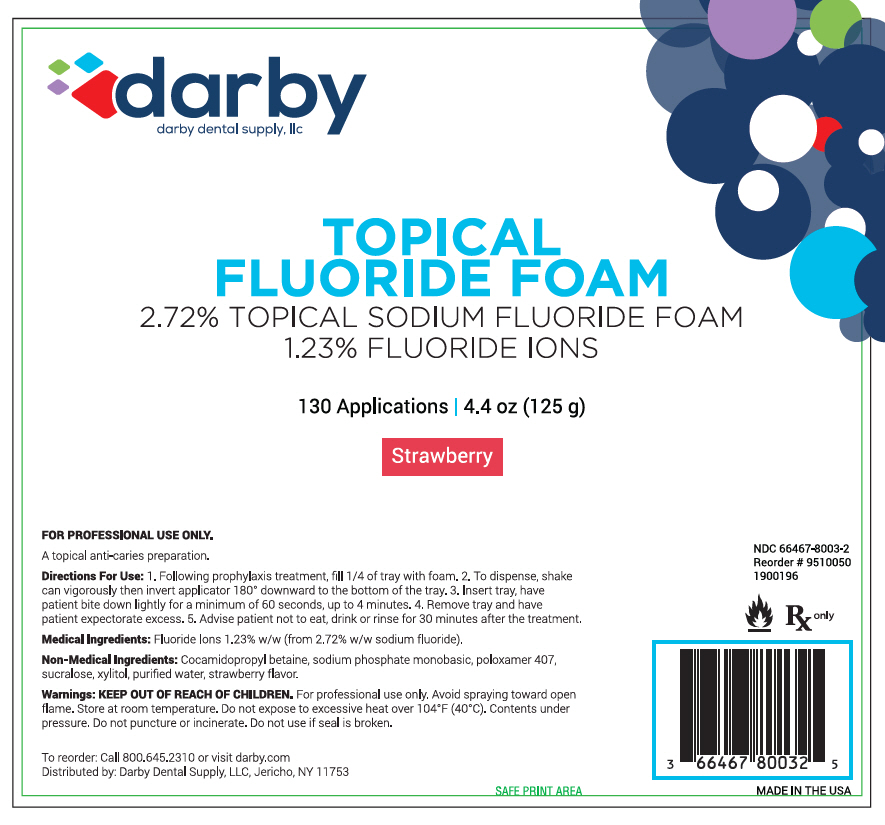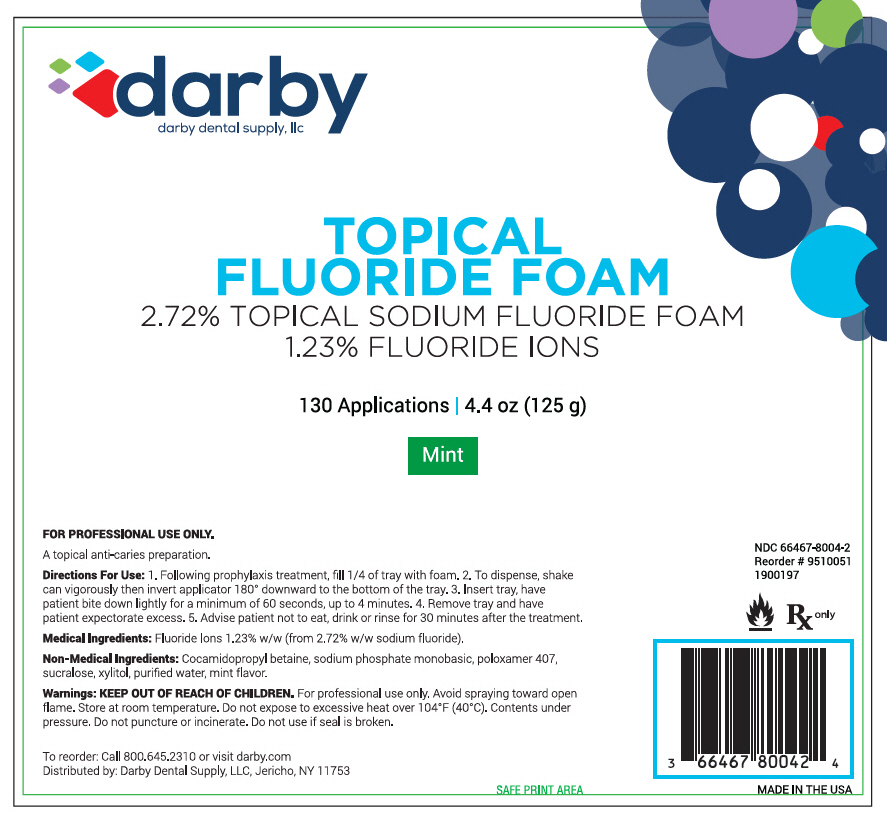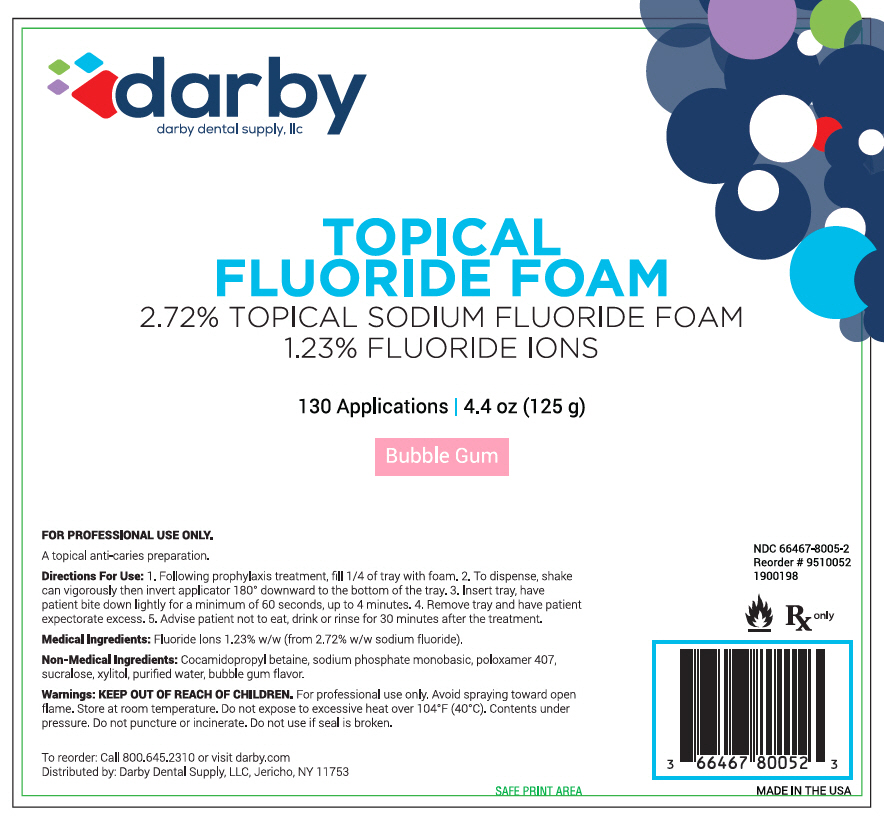 DRUG LABEL: DARBY APF STRAWBERRY
NDC: 66467-8003 | Form: AEROSOL, FOAM
Manufacturer: Darby Dental Supply, LLC
Category: prescription | Type: HUMAN PRESCRIPTION DRUG LABEL
Date: 20230112

ACTIVE INGREDIENTS: SODIUM FLUORIDE 2.72 g/100 g
INACTIVE INGREDIENTS: WATER; Sucralose; Xylitol; SODIUM PHOSPHATE, MONOBASIC, ANHYDROUS; COCAMIDOPROPYL BETAINE; STRAWBERRY; POLOXAMER 407

FLUORIDE FOAM

Strawberry

FOR PROFESSIONAL USE ONLY. A topical anti-caries preparation.

Directions For Use

l. Following prophylaxis treatment, fill l/4 of tray with foam. 2. To dispense, shake can vigorously then invert applicator 180° downward to the bottom of the tray. 3. Insert tray, have patient bite down lightly for a minimum of 60 seconds, up to 4 minutes. 4. Remove tray and have patient expectorate excess. 5. Advise patient not to eat, drink or rinse for 30 minutes after the treatment.

Medical Ingredients

Fluoride Ions 1.23% w/w (from 2.72% w/w sodium fluoride).

Non-Medical Ingredients

Cocamidopropyl betaine, sodium phosphate monobasic, poloxamer 407, sucralose, xylitol, purified water, strawberry flavor.

Warnings

KEEP OUT OF REACH OF CHILDREN. For professional use only. Avoid spraying toward open flame. Store at room temperature. Do not expose to excessive heat over 104° F (40°C). Contents under pressure. Do not puncture or incinerate. Do not use if seal is broken.

To reorder: Call 800.645.2310 or visit darby.com

Distributed by: Darby Dental Supply, LLC, Jericho, NY 11753

NDC 66467-8003∙2

Reorder# 9510050

1900196

Mint

FOR PROFESSIONAL USE ONLY. A topical anti-caries preparation.

Directions For Use

l. Following prophylaxis treatment, fill l/4 of tray with foam. 2. To dispense, shake can vigorously then invert applicator 180° downward to the bottom of the tray. 3. Insert tray, have patient bite down lightly for a minimum of 60 seconds, up to 4 minutes. 4. Remove tray and have patient expectorate excess. 5. Advise patient not to eat, drink or rinse for 30 minutes after the treatment.

Medical Ingredients

Fluoride Ions 1.23% w/w (from 2.72% w/w sodium fluoride).

Non-Medical Ingredients

Cocamidopropyl betaine, sodium phosphate monobasic, poloxamer 407, sucralose, xylitol, purified water, mint flavor.

Warnings

KEEP OUT OF REACH OF CHILDREN. For professional use only. Avoid spraying toward open flame. Store at room temperature. Do not expose to excessive heat over 104° F (40°C). Contents under pressure. Do not puncture or incinerate. Do not use if seal is broken.

To reorder: Call 800.645.2310 or visit darby.com

Distributed by: Darby Dental Supply, LLC, Jericho, NY 11753

NDC 66467-8004∙2

Reorder# 9510051

1900197

Bubble Gum

FOR PROFESSIONAL USE ONLY. A topical anti-caries preparation.

Directions For Use

l. Following prophylaxis treatment, fill l/4 of tray with foam. 2. To dispense, shake can vigorously then invert applicator 180° downward to the bottom of the tray. 3. Insert tray, have patient bite down lightly for a minimum of 60 seconds, up to 4 minutes. 4. Remove tray and have patient expectorate excess. 5. Advise patient not to eat, drink or rinse for 30 minutes after the treatment.

Medical Ingredients

Fluoride Ions 1.23% w/w (from 2.72% w/w sodium fluoride).

Non-Medical Ingredients

Cocamidopropyl betaine, sodium phosphate monobasic, poloxamer 407, sucralose, xylitol, purified water, bubble gum flavor.

Warnings

KEEP OUT OF REACH OF CHILDREN. For professional use only. Avoid spraying toward open flame. Store at room temperature. Do not expose to excessive heat over 104° F (40°C). Contents under pressure. Do not puncture or incinerate. Do not use if seal is broken.

To reorder: Call 800.645.2310 or visit darby.com

Distributed by: Darby Dental Supply, LLC, Jericho, NY 11753

NDC 66467-8005∙2

Reorder# 9510052

1900198

PRINCIPAL DISPLAY PANEL - 125 g Can Label - Strawberry

darby
darby dental supply, llc

TOPICAL
FLUORIDE FOAM
2.72% TOPICAL SODIUM FLUORIDE FOAM
1.23% FLUORIDE IONS

130 Applications | 4.4 oz (125 g)

Strawberry

PRINCIPAL DISPLAY PANEL - 125 g Can Label - Mint

darby
darby dental supply, llc

TOPICAL
FLUORIDE FOAM
2.72% TOPICAL SODIUM FLUORIDE FOAM
1.23% FLUORIDE IONS

130 Applications | 4.4 oz (125 g)

Mint

PRINCIPAL DISPLAY PANEL - 125 g Can Label - Bubble Gum

darby
darby dental supply, llc

TOPICAL
FLUORIDE FOAM
2.72% TOPICAL SODIUM FLUORIDE FOAM
1.23% FLUORIDE IONS

130 Applications | 4.4 oz (125 g)

Bubble Gum